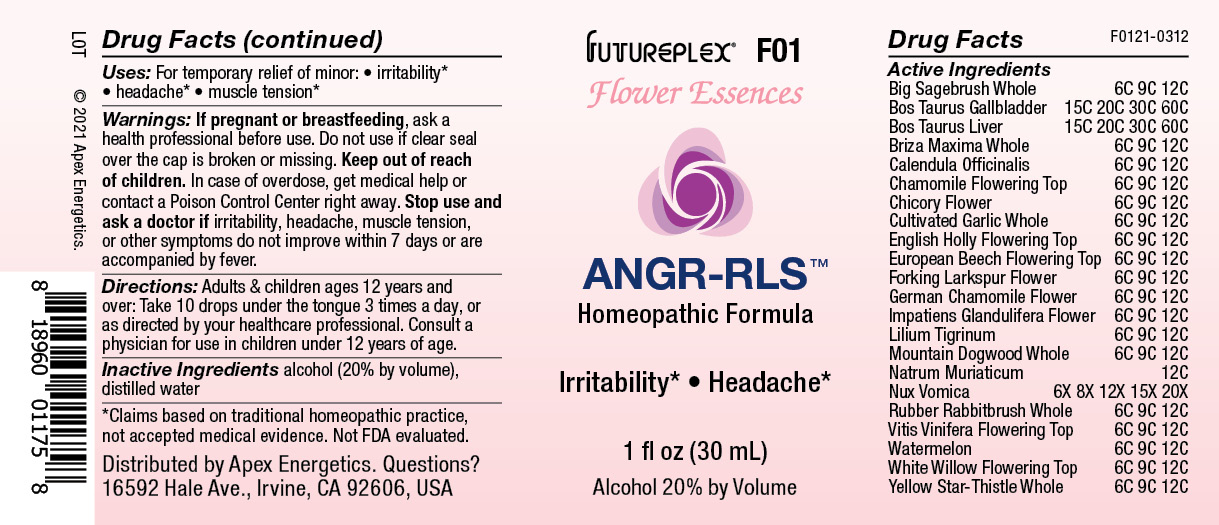 DRUG LABEL: F01
NDC: 63479-0601 | Form: SOLUTION/ DROPS
Manufacturer: Apex Energetics Inc.
Category: homeopathic | Type: HUMAN OTC DRUG LABEL
Date: 20240108

ACTIVE INGREDIENTS: ARTEMISIA TRIDENTATA WHOLE 12 [hp_C]/1 mL; BOS TAURUS GALLBLADDER 60 [hp_C]/1 mL; BEEF LIVER 60 [hp_C]/1 mL; BRIZA MAXIMA WHOLE 12 [hp_C]/1 mL; CALENDULA OFFICINALIS FLOWERING TOP 12 [hp_C]/1 mL; CICHORIUM INTYBUS FLOWER 12 [hp_C]/1 mL; ALLIUM SATIVUM WHOLE 12 [hp_C]/1 mL; ILEX AQUIFOLIUM FLOWERING TOP 12 [hp_C]/1 mL; CONSOLIDA REGALIS FLOWER 12 [hp_C]/1 mL; IMPATIENS GLANDULIFERA FLOWER 12 [hp_C]/1 mL; LILIUM LANCIFOLIUM WHOLE FLOWERING 12 [hp_C]/1 mL; SODIUM CHLORIDE 12 [hp_C]/1 mL; STRYCHNOS NUX-VOMICA SEED 20 [hp_X]/1 mL; ERICAMERIA NAUSEOSA WHOLE 12 [hp_C]/1 mL; VITIS VINIFERA FLOWERING TOP 12 [hp_C]/1 mL; WATERMELON 12 [hp_C]/1 mL; SALIX ALBA FLOWERING TOP 12 [hp_C]/1 mL; CENTAUREA SOLSTITIALIS WHOLE 12 [hp_C]/1 mL; MATRICARIA RECUTITA FLOWERING TOP 12 [hp_C]/1 mL; FAGUS SYLVATICA FLOWERING TOP 12 [hp_C]/1 mL; CHAMOMILE 12 [hp_C]/1 mL; CORNUS NUTTALLII WHOLE 12 [hp_C]/1 mL
INACTIVE INGREDIENTS: WATER; ALCOHOL

F01

Active Ingredients
Big Sagebrush Whole | 6C 9C 12C
Bos Taurus Gallbladder | 15C 20C 30C 60C
Bos Taurus Liver | 15C 20C 30C 60C
Briza Maxima Whole | 6C 9C 12C
Calendula Officinalis | 6C 9C 12C
Chamomile Flowering Top | 6C 9C 12C
Chicory Flower | 6C 9C 12C
Cultivated Garlic Whole | 6C 9C 12C
English Holly Flowering Top | 6C 9C 12C
European Beech Flowering Top | 6C 9C 12C
Forking Larkspur Flower | 6C 9C 12C
German Chamomile Flower | 6C 9C 12C
Impatiens Glandulifera Flower | 6C 9C 12C
Lilium Tigrinum | 6C 9C 12C
Mountain Dogwood Whole | 6C 9C 12C
Natrum Muriaticum | 12C
Nux Vomica | 6X 8X 12X 15X 20X
Rubber Rabbitbrush Whole | 6C 9C 12C
Vitis Vinifera Flowering Top | 6C 9C 12C
Watermelon | 6C 9C 12C
White Willow Flowering Top | 6C 9C 12C
Yellow Star-Thistle Whole | 6C 9C 12C

INDICATIONS AND USAGE

Uses:

For temporary relief of minor:

irritability*

headache*

muscle tension*

*Claims based on traditional homeopathic practice, not accepted medical evidence. Not FDA evaluated.

Warnings:

PREGNANCY OR BREAST FEEDING

If pregnant or breastfeeding, ask a health professional before use.

Do not use if clear seal over the cap is broken or missing.

Keep out of reach of children. In case of overdose, get medical help or contact a Poison Control Center right away.

Stop use and ask a doctor if irritability, headache, muscle tension, or other symptoms do not improve within 7 days or are accompanied by fever.

Directions:

Adults & children ages 12 years and over: Take 10 drops under the tongue 3 times a day, or as directed by your healthcare professional. Consult a physician for use in children under 12 years of age.

Inactive Ingredients

alcohol (20% by volume), distilled water

Distributed by Apex Energetics. Questions?

16592 Hale Ave., Irvine, CA 92606, USA

PACKAGE LABEL

FUTUREPLEX® F01

FLOWER ESSENCES

ANGR-RLS™

Homeopathic Formula

Irritability*

Headache*

1 fl oz (30 mL)

Alcohol 20% by Volume